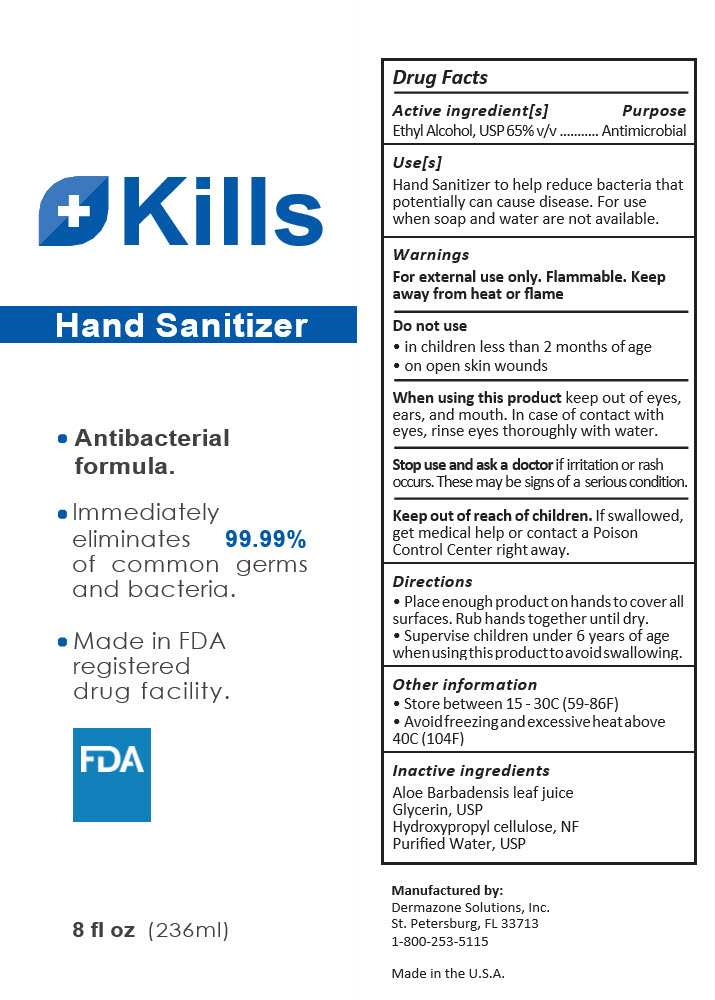 DRUG LABEL: Kills Hand Sanitizer
NDC: 58466-105 | Form: GEL
Manufacturer: Dermazone LLC
Category: otc | Type: HUMAN OTC DRUG LABEL
Date: 20250725

ACTIVE INGREDIENTS: ALCOHOL 65 mL/100 mL
INACTIVE INGREDIENTS: ALOE VERA LEAF; GLYCERIN; HYDROXYPROPYL CELLULOSE, UNSPECIFIED; WATER

Kills Hand Sanitizer Gel

Drug Facts

Active ingredient[s]

Ethyl Alcohol, USP 65% v/v

Purpose

Antimicrobial

Use[s]

Hand Sanitizer to help reduce bacteria that potentially can cause disease. For use when soap and water are not available.

Warnings

For external use only. Flammable. Keep away from heat or ﬂame

Do not use

- in children less than 2 months of age
- on open skin wounds

When using this product keep out of eyes, ears, and mouth. In case of contact with eyes, rinse eyes thoroughly with water.

Stop use and ask a doctor if irritation or rash occurs. These may be signs of a serious condition.

Keep out of reach of children. If swallowed, get medical help or contact a Poison Control Center right away.

Directions

- Place enough product on hands to cover all surfaces. Rub hands together until dry.
- Supervise children under 6 years of age when using this product to avoid swallowing.

Other information

- Store between 15 - 30C (59-86F)
- Avoid freezing and excessive heat above 40C (104F)

Inactive ingredients

Aloe Barbadensis leaf juice

Glycerin, USP

Hydroxypropyl cellulose, NF

Puriﬁed Water, USP

Manufactured by:

Dermazone Solutions, Inc.
St. Petersburg, FL 33713

PRINCIPAL DISPLAY PANEL - 236 mL Bottle Label

Kills

Hand Sanitizer

- Antibacterial
  formula.
- Immediately eliminates 99.99%
  of common germs
  and bacteria.
- Made in FDA
  registered
  drug facility.

FDA

8 fl oz (236ml)